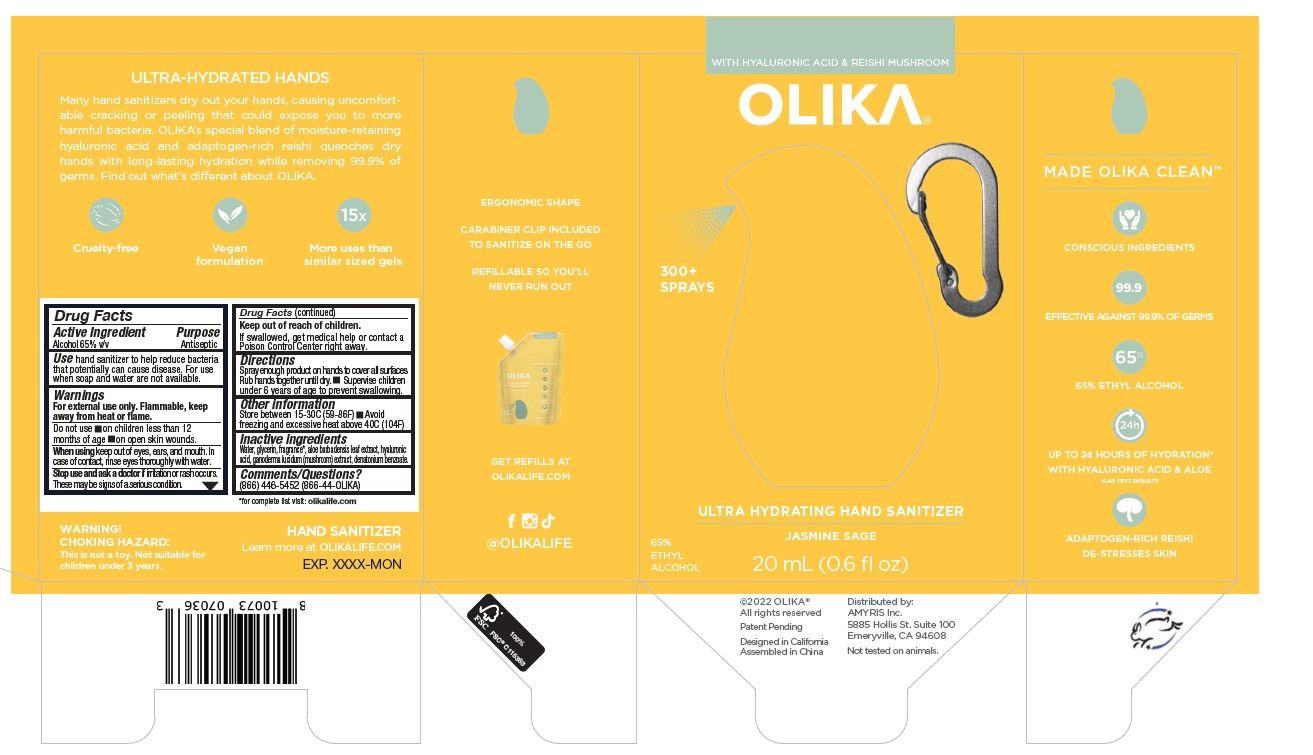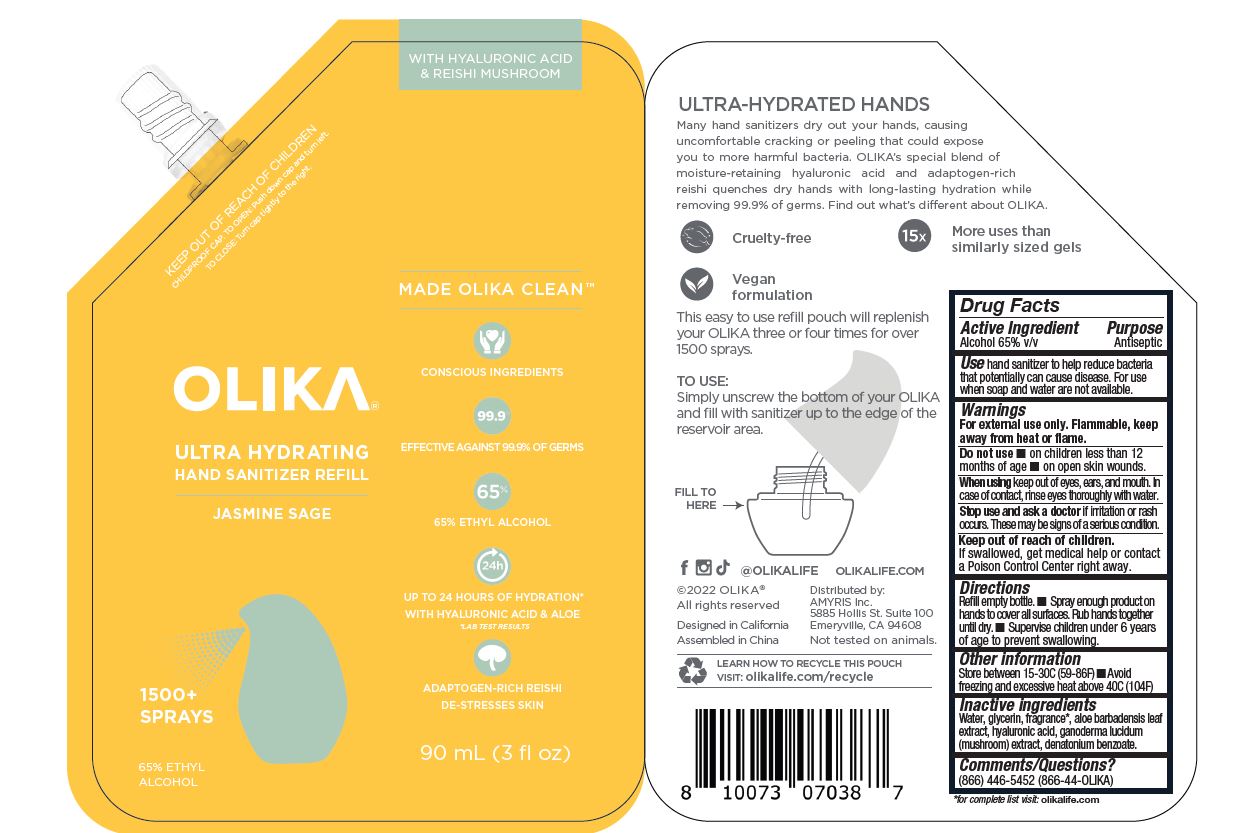 DRUG LABEL: OLIKA Hydrating Hand Sanitizer-Jasmine Sage
NDC: 73517-848 | Form: GEL
Manufacturer: Amyris
Category: otc | Type: HUMAN OTC DRUG LABEL
Date: 20220729

ACTIVE INGREDIENTS: ALCOHOL 65 mL/100 mL
INACTIVE INGREDIENTS: GLYCERIN; ALOE VERA LEAF; DENATONIUM BENZOATE; HYALURONIC ACID; WATER; GANODERMA LUCIDUM STEM; FRAGRANCE 13576

OLIKA Hydrating Hand Sanitizer- Jasmine Sage

ACTIVE INGREDIENT

Ethyl Alcohol 65% v/v. Purpose: Antiseptic

PURPOSE

Antiseptic, Hand Sanitizer

INDICATIONS AND USAGE

Hand Sanitizer to help reduce bacteria that potentially can cause disease. For use when soap and water are not available.

WARNINGS

For external use only. Flammable. Keep away from heat or flame

DO NOT USE

in children less than 2 months of age
on open skin wounds

When using this product keep out of eyes, ears, and mouth. In case of contact with eyes, rinse eyes thoroughly with water.

Stop use and ask a doctor if irritation or rash occurs. These may be signs of a serious condition.

Keep out of reach of children. If swallowed, get medical help or contact a Poison Control Center right away.

DOSAGE AND ADMINISTRATION

Place enough product on hands to cover all surfaces. Rub hands together until dry.
Supervise children under 6 years of age when using this product to avoid swallowing.

STORAGE AND HANDLING

Store between 15-30C (59-86F)
Avoid freezing and excessive heat above 40C (104F)

INACTIVE INGREDIENT

water, glycerin, fragrance, aloe barbadensis leaf extract, hyaluronic acid, ganoderma lucidum (mushroom) extract, denatonium benzoate

PACKAGE LABEL

90 ML NDC# 73517-848-01

20 ML NDC# 73517-848-02